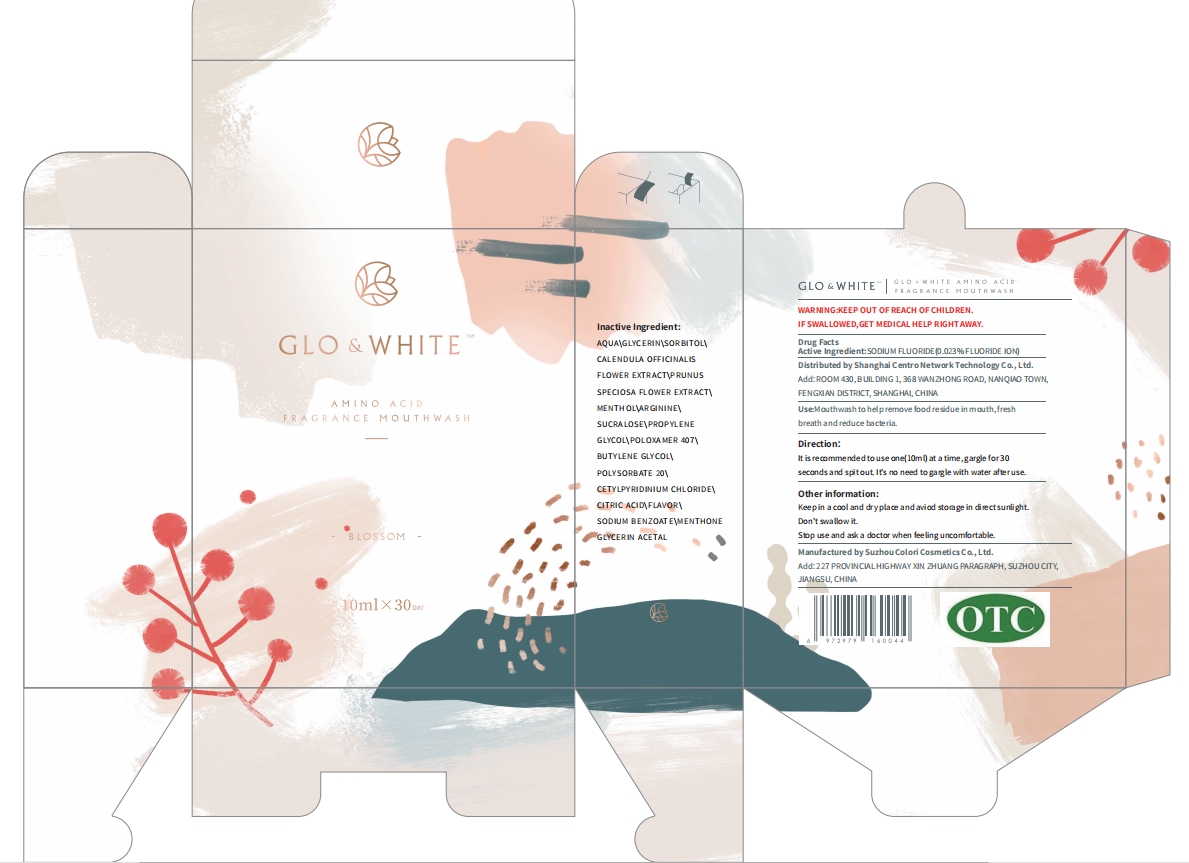 DRUG LABEL: AMINO ACID FRAGRANCEMOUTHWASH BLOSSOM
NDC: 55409-001 | Form: LIQUID
Manufacturer: Shanghai Centro Network Technology Co., Ltd.
Category: otc | Type: HUMAN OTC DRUG LABEL
Date: 20201009

ACTIVE INGREDIENTS: SODIUM FLUORIDE 0.005 g/10 mL
INACTIVE INGREDIENTS: WATER; GLYCERIN; CALENDULA OFFICINALIS FLOWER; ARGININE; PROPYLENE GLYCOL; CETYLPYRIDINIUM CHLORIDE; METHYL SALICYLATE; SORBITOL; POLOXAMER 407; BUTYLENE GLYCOL; SODIUM BENZOATE; MENTHONE 1,2-GLYCEROL KETAL, (+/-)-; PRUNUS SPECIOSA FLOWER; SUCRALOSE; MENTHOL; POLYSORBATE 20; CITRIC ACID MONOHYDRATE

DOSAGE AND ADMINISTRATION

Keep in a cool and dry place and aviod storage in direct sunlight.

INACTIVE INGREDIENT

AQUA、GLYCERIN、SORBITOL、CALENDULA OFFICINALIS FLOWER EXTRACT、PRUNUS SPECIOSA FLOWER EXTRACT、MENTHOL、ARGININE、SUCRALOSE、PROPYLENE GLYCOL、POLOXAMER 407、BUTYLENE GLYCOL、POLYSORBATE 20、CETYLPYRIDINIUM CHLORIDE、 CITRIC ACID、FLAVOR、SODIUM BENZOATE、MENTHONE GLYCERIN ACETAL

INDICATIONS AND USAGE

It is recommended to use one(10ml) at a time, gargle for 30 seconds and spit out It's no need to garglewith water after use.

ACTIVE INGREDIENT

SODIUM FLUORIDE

DO NOT USE

Don't swallow it.

keep out of reach of children

PURPOSE

gargle

WARNINGS

Stopuse and aska doctor when feelinguncomfortable.